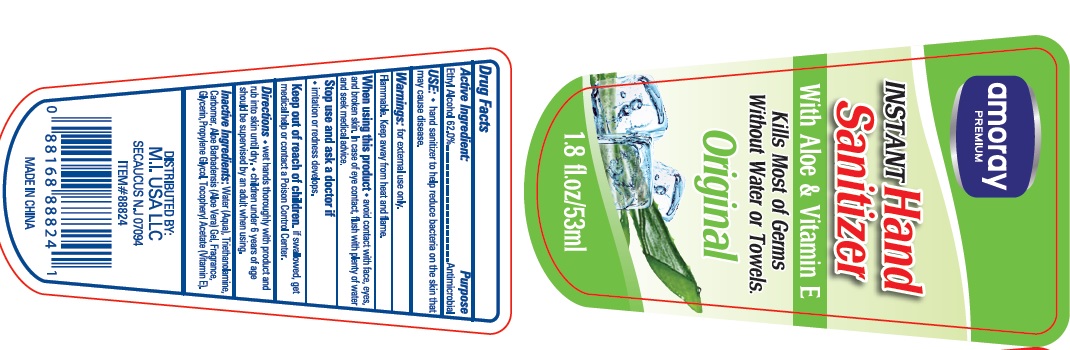 DRUG LABEL: amoray premium instant hand sanitizer with aloe and vitamin e
NDC: 73344-108 | Form: GEL
Manufacturer: NINGBO SANTE YING MEDICALAND HEALTHDEVELOPMENT CO.,LTD
Category: otc | Type: HUMAN OTC DRUG LABEL
Date: 20190929

ACTIVE INGREDIENTS: alcohol 62 mL/100 mL
INACTIVE INGREDIENTS: WATER; PROPYLENE GLYCOL; ALOE VERA LEAF; CARBOMER 934; GLYCERIN; .ALPHA.-TOCOPHEROL ACETATE, D-; TROLAMINE

Drug facts

Active ingredient Purpose

Ethyl Alcohol 62% ... Antimicrobial

PURPOSE

Hand sanitizer to help decrease bacteria on the skin that may cause disease.

KEEP OUT OF REACH OF CHILDREN

If swallowed, get medical help or contact local poison control center right away.

Children must be supervised in use of this product.

INDICATIONS AND USAGE

keep out of eyes

when water, soap and towel are not available

WARNINGS

For external use only.
Flammable. Keep away from hear or flame.

Do not apply around eyes; Do not use in ears and mouth. When using this products, avoid contact with eyes. In case of contact, flush eyes with water.

Stop using and ask a doctor, if irritation and redness develops, if condition persists for more than 72 hours, consult a doctor.

DOSAGE AND ADMINISTRATION

Pump as needed into your palms and thoroughly spread on both hands, and rub the skin until dry.

Children under 6 years of age should be supervised by an adult when using.

INACTIVE INGREDIENT

Water, Carbomer, Glycerin, Propylene Glycol, Triethanolamine, Aloe Barbadensis Leaf Juice, Tocopheryl Acetate (Vitamin E), Fragrance